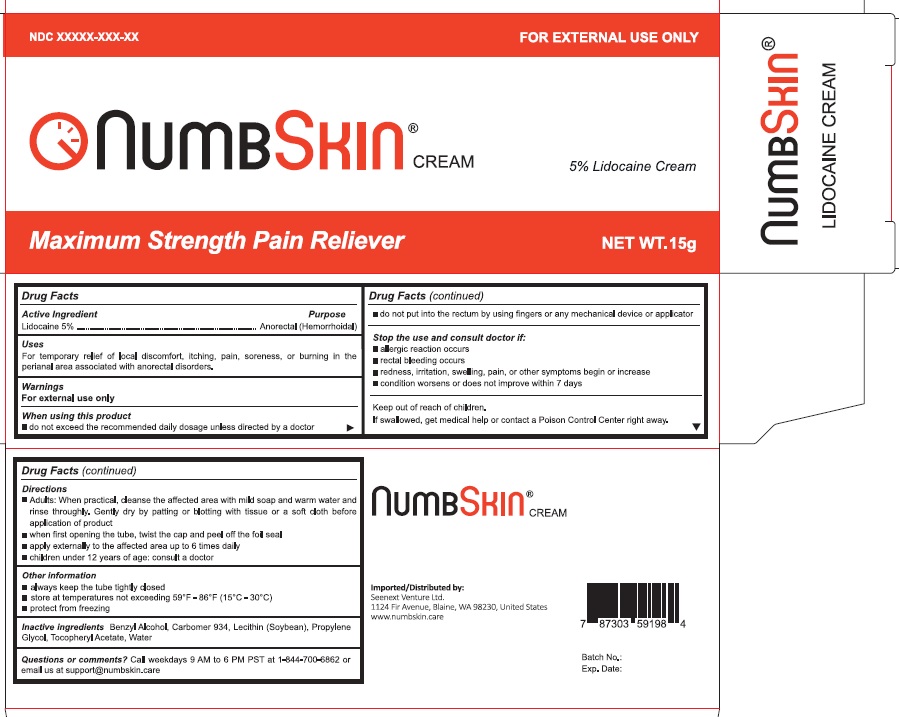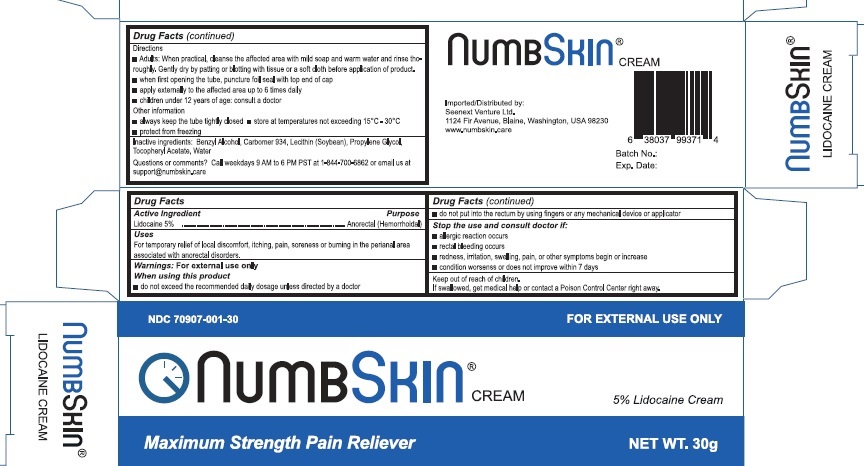 DRUG LABEL: Numb Skin

NDC: 70907-001 | Form: CREAM
Manufacturer: Seenext Venture Ltd
Category: otc | Type: HUMAN OTC DRUG LABEL
Date: 20221109

ACTIVE INGREDIENTS: LIDOCAINE 5 mg/30 g
INACTIVE INGREDIENTS: WATER; CARBOMER 934; PROPYLENE GLYCOL BUTYL ETHER; TOCOPHERYL RETINOATE; BENZYL ALCOHOL; LECITHIN, SOYBEAN

Drug Facts

Active Ingredient

Lidocaine 5%

Purpose

Anorectal (Hemmorhoidal)

Uses

For temporary relief of local discomfort, itching, pain, soreness or burning in the perianal area associated with anorectal disorders.

Warnings

For external use only

When using this product

- do not exceed the recommended daily dosage unless directed by a doctor
- do not put into the rectum by using fingers or any mechanical device or applicator

Stop the use and consult doctor if:

- allergic reaction occurs
- rectal bleeding occurs
- redness, irritation, swelling, pain, or other symptoms begin or increase
- condition worsenss or does not improve within 7 days

Keep out of reach of children

If swallowed, get medical help or contact a Poison Control Center right away

Directions

- Adults: When practical, cleanse the affected area with mild soap and warm water and rinse thoroughly. Gently dry by patting or blotting with tissue or a soft cloth before application of product.
- when first opening the tube, puncture foil seal with top end of cap
- apply externally to the affected area up to 6 times daily
- children under 12 years of age: consult a doctor

Other information

- always keep the tube tightly closed
- store at temperatures not exceeding 15OC - 30OC
- protect from freezing

Inactive ingrdients

Benzyl Alcohol, Carbomer 934, Lecithin (Soybean), Propylene Glycol, Tocopheryl Acetate, Water

Question or comments

Call weekdays 9 AM to 6 PM PST at 1-844-700-6862 or email us at support@numbskin.com

Principal Display Panel

NDC 70907-001-15

FOR EXTERNAL USE ONLY

NumbSkin Cream®

5% Lidocaine Cream

Maximum Strength Pain Reliever

NET WT. 15g

NDC 70907-001-30

FOR EXTERNAL USE ONLY

NumbSkin Cream®

5% Lidocaine Cream

Maximum Strength Pain Reliever

NET WT. 30g